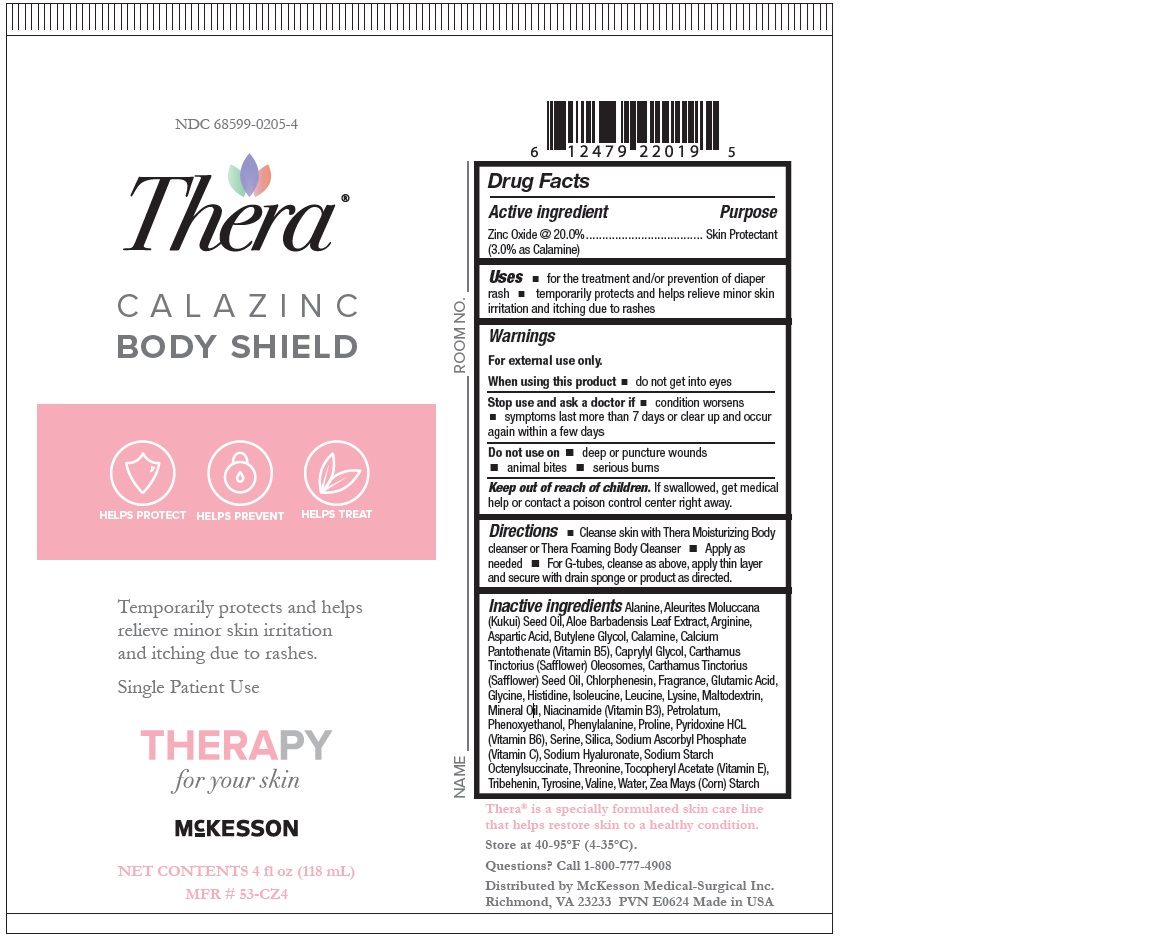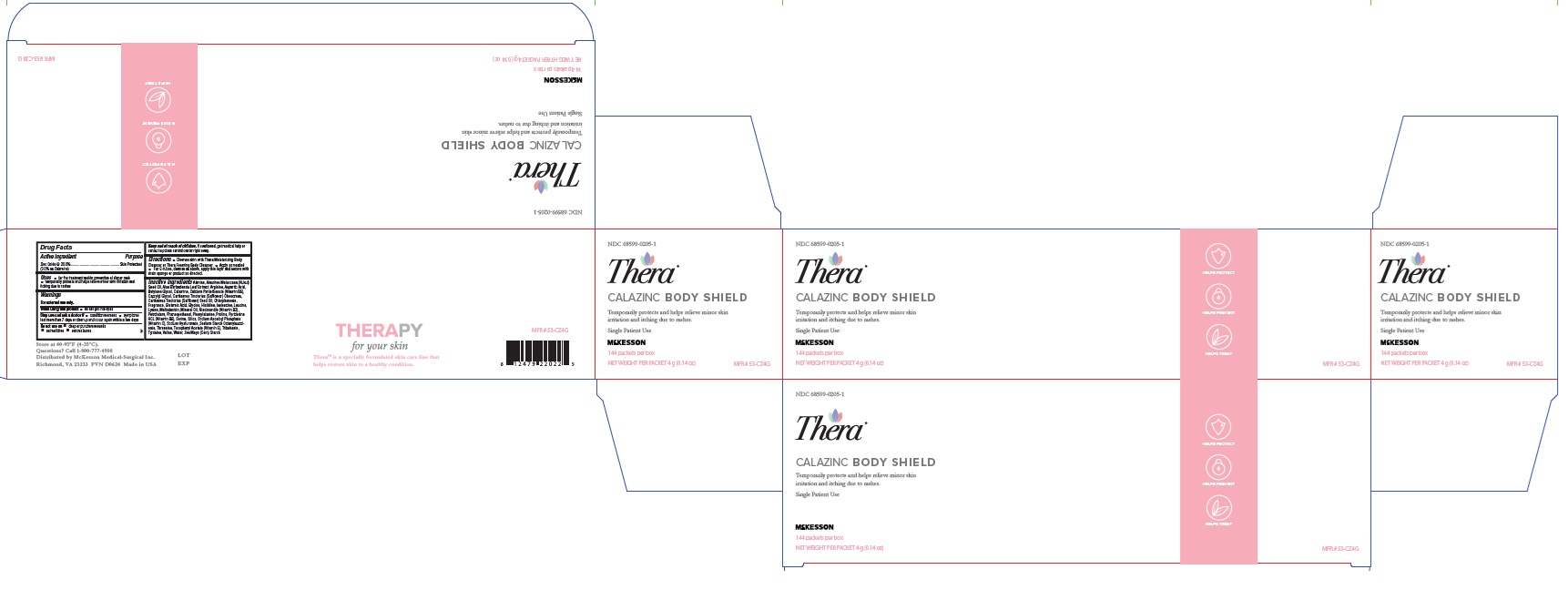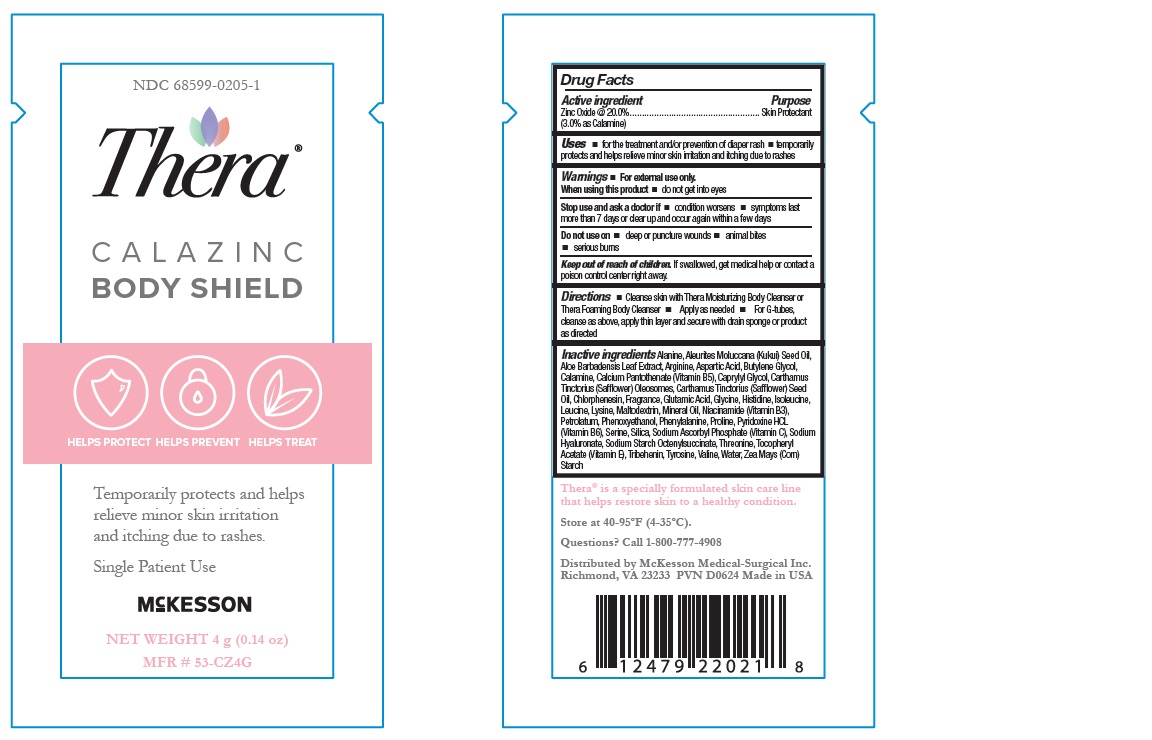 DRUG LABEL: THERA Calazinc Body Shield
NDC: 68599-0205 | Form: PASTE
Manufacturer: McKesson Medical-Surgical Inc.
Category: otc | Type: HUMAN OTC DRUG LABEL
Date: 20240617

ACTIVE INGREDIENTS: ZINC OXIDE 200 mg/1 g
INACTIVE INGREDIENTS: HISTIDINE; TYROSINE; LYSINE; ISOLEUCINE; KUKUI NUT OIL; ALOE VERA LEAF; CALCIUM PANTOTHENATE; MALTODEXTRIN; NIACINAMIDE; PYRIDOXINE HYDROCHLORIDE; SILICON DIOXIDE; .ALPHA.-TOCOPHEROL ACETATE, DL-; LEVOMENOL; SAFFLOWER OIL; PETROLATUM; HYALURONATE SODIUM; GINGER; ASPARTIC ACID; ALANINE; PROLINE; MINERAL OIL; VALINE; WATER; SERINE; CHLORPHENESIN; OCTENYLSUCCINIC ACID; GLYCINE; CAPRYLYL GLYCOL; CARTHAMUS TINCTORIUS SEED OLEOSOMES; PHENYLALANINE; ZEA MAYS WHOLE; LEUCINE; ARGININE; BUTYLENE GLYCOL; ZINC CARBONATE; THREONINE; GLUTAMIC ACID

Drug Facts

Active ingredient

- Zinc Oxide 20.0% (3.0% as Calamine)

Purpose

- Skin Protectant

Keep out of reach of children.

- If swallowed, get medical help or contact a Poison Control Center right away.

Uses

- For the treatment and/or prevention of diaper rash
- temporarily protects and helps relieve minor skin irritation and itching due to rashes

Warnings

- For external use only

Do not use on

- deep or puncture wounds
- animal bites
- serious burns

When using this product

- do not get into eyes

Stop use and ask a doctor if

- condition worsens
- symptoms last more than 7 days or clear up and occur again within a few days

Directions

- Cleanse skin with THERATMMoisturizing Body Cleanser or THERATMFoaming Body Cleanser
- Apply paste to area as needed
- For G-tubes, cleanse as above, apply thin layer and secure with drain sponge or product as directed

Other information

- Protect from freezing. Avoid excessive heat.

INACTIVE INGREDIENT

- Aleurites Moluccana Seed Oil,
- Aloe Barbadensis (Aloe Vera) Leaf Juice,
- SAFFLEXTM(Consisting of: Calcium Pantothenate (Vitamin B5),
- Maltodexdrin,
- Niacinamide (Vitamin B3),
- Pyridoxine HCl (Vitamin B6),
- Silica,
- Sodium Ascorbyl Phosphate (Vitamin C),
- Sodium Starch Octenylsuccinate,
- Tocopheryl Acetate (Vitamin E)), Bisabolol,
- Carthamus Tinctorius (Safflower) Olesomes,
- Carthamus Tinctorius (Safflower) Seed Oil,
- Lavender Ylang Fragrance,
- Modified Corn Starch,
- Pentaerythrityl Tetra-di-t-Butyl Hydroxyhydrocinnamate,
- Petrolatum,
- Phenoxyethanol,
- Sodium Hyaluronate,
- Zingiber Officinale (Ginger) Root Extract.

Label (4 oz)

NDC 68599-0205-4

Thera

Calazinc Body Shield

Net Contents 4 fl oz (113 mL)

MFR# 53-CZ4

Label(4 g)

NDC 68599-0205-1

Thera

Calazinc Body Shield

Net Weight 4 g (0.14 oz)

MFR# 53-CZ4G